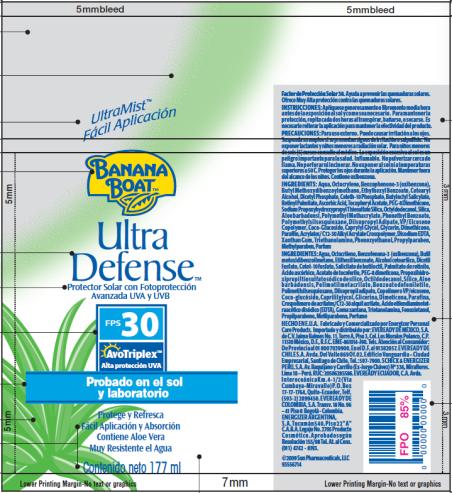 DRUG LABEL: Banana Boat Ultra Defense SPF 30 for LATAM
NDC: 17630-2023 | Form: SPRAY
Manufacturer: Accra-Pac, Inc.
Category: otc | Type: HUMAN OTC DRUG LABEL
Date: 20100326

ACTIVE INGREDIENTS: HOMOSALATE 0.0878 mL/1 mL; OCTINOXATE 0.05 mL/1 mL; OCTISALATE 0.05 mL/1 mL; OCTOCRYLENE 0.025 mL/1 mL; OXYBENZONE 0.05 mL/1 mL; AVOBENZONE 0.03 mL/1 mL
INACTIVE INGREDIENTS: CETOSTEARYL ALCOHOL; DIHEXADECYL PHOSPHATE; VITAMIN A PALMITATE; ASCORBIC ACID; .ALPHA.-TOCOPHEROL ACETATE, D-; OCTYLDODECANOL; SILICON DIOXIDE; DIISOPROPYL ADIPATE; CAPRYLYL GLYCOL; GLYCERIN; DIMETHICONE; PARAFFIN; EDETATE DISODIUM; XANTHAN GUM; TROLAMINE; PHENOXYETHANOL; PROPYLPARABEN; METHYLPARABEN; ALOE VERA LEAF

Banana Boat Ultra Defense SPF 30 for LATAM

Active Ingredients

Homosalate 0.0878mL / 1mL

Octinoxate 0.05mL / 1mL

Octisalate 0.05mL / 1mL

Octocrylene 0.025mL / 1mL

Oxybenzone 0.05mL / 1mL

Avobenzone 0.03mL / 1mL

INSTRUCCIONES:

Aplíquese generosamente o libremente media hora antes de la exposición al sol y como sea necesario. Para mantener la protección, repita cada dos horas al transpirar, bañarse, o secarse. Es necesario reiterar la aplicación para mantener la efectividad del producto.

PRECAUCIONES:

Para uso externo. Puede causar irritación a los ojos. Suspenda su empleo si se presentan signos de irritación o salpullido. No exponer lactantes y niños menores a radiación solar. Para niños menores de seis (6) meses consulte al médico. La exposición excesiva al sol es un peligro importante para la salud. Inflamable. No pulverizar cerca de llama. No perforar ni incinerar. No exponer al sol ni a temperaturas superiores a 50 C. Proteger los ojos durante la aplicación. Mantener fuera del alcance de los niños. Contiene oxibenzona.

INGREDIENTS:

Aqua, Octocrylene, Benzophenone-3 (oxibenzona), Butyl Methoxydibenzoylmethane, Ethylhexyl Benzoate, Cetearyl Alcohol, Dicetyl Phosphate, Ceteth-10 Phosphate, Butyloctyl Salicylate, Retinyl Palmitate, Ascorbic Acid, Tocopheryl Acetate, PEG-8 Dimethicone, Sodium Propoxyhydroxypropyl Thiosulfate Silica, Octyldodecanol, Silica, Aloe barbadensi, Polymethyl Methacrylate, Phenethyl Benzoate, Polymethylsilsesquioxane, Diisopropyl Adipate, VP/Eicosene Copolymer, Coco-Glucoside, Caprylyl Glycol, Glycerin, Dimethicone, Paraffin, Acrylates/ C12-30 Alkyl Acrylate Crosspolymer, Disodium EDTA, Xanthan Gum, Triethanolamine, Phenoxyethanol, Propylparaben, Methylparaben, Parfum

INGREDIENTES:

Agua, Octocrileno, Benzofenona-3 (oxibenzona), Butil metoxidibenzoilmetano, Etilhexil benzoate, Alcohol cetearílico, Dicetil fosfato, Cetet-10 fosfato, Salicilato de butiloctil, Palmitato de retinilo, Ácido ascórbico, Acetato de tocoferilo, PEG-8 dimeticona, Propoxihidroxipropil tiosulfato sódico de sílice, Octildodecanol, Sílice, Aloe barbadensis, Polimetil met acrilato, Benzoato de fenil etilo, Polimetilsilsesquioxano, Diisopropil adipato, Copolímero VP/eicosene, Coco-glucósido, Caprilil glycol, Glicerina, Dimeticona, Parafina, Crospolímero de acrilatos/C12-30 alquil acrilato, Ácido etilendiaminotetraacético disódico (EDTA), Goma xantana, Trietanolamina, Fenoxietanol, Propilparabeno, Metilparabeno, Perfume

Distributed by:
ENERGIZER ARGENTINA,
S.A.Tucumán 540, Piso 22 "A"
C.A.B.A. Legajo No. 2705 Producto
Cosmético. Aprobado según
Resolución 155/98 Tel. At. al Cons.
(011) 4742 - 8193.

PRINCIPAL DISPLAY PANEL

UltraMist TM
Fácil Aplicación
BANANA
BOATTM
Ultra Defense
Protector Solar con Fotoprotección
Avanzada UVA y UVB
FPS 30
AvoTriplex TM
Alta protección UVA
Probado en el sol
y laboratorio
Protege y Refresca
Fácil Aplicación y Absorción
Contiene Aloe Vera
Muy Resistente el Agua
Contenido neto 177 ml